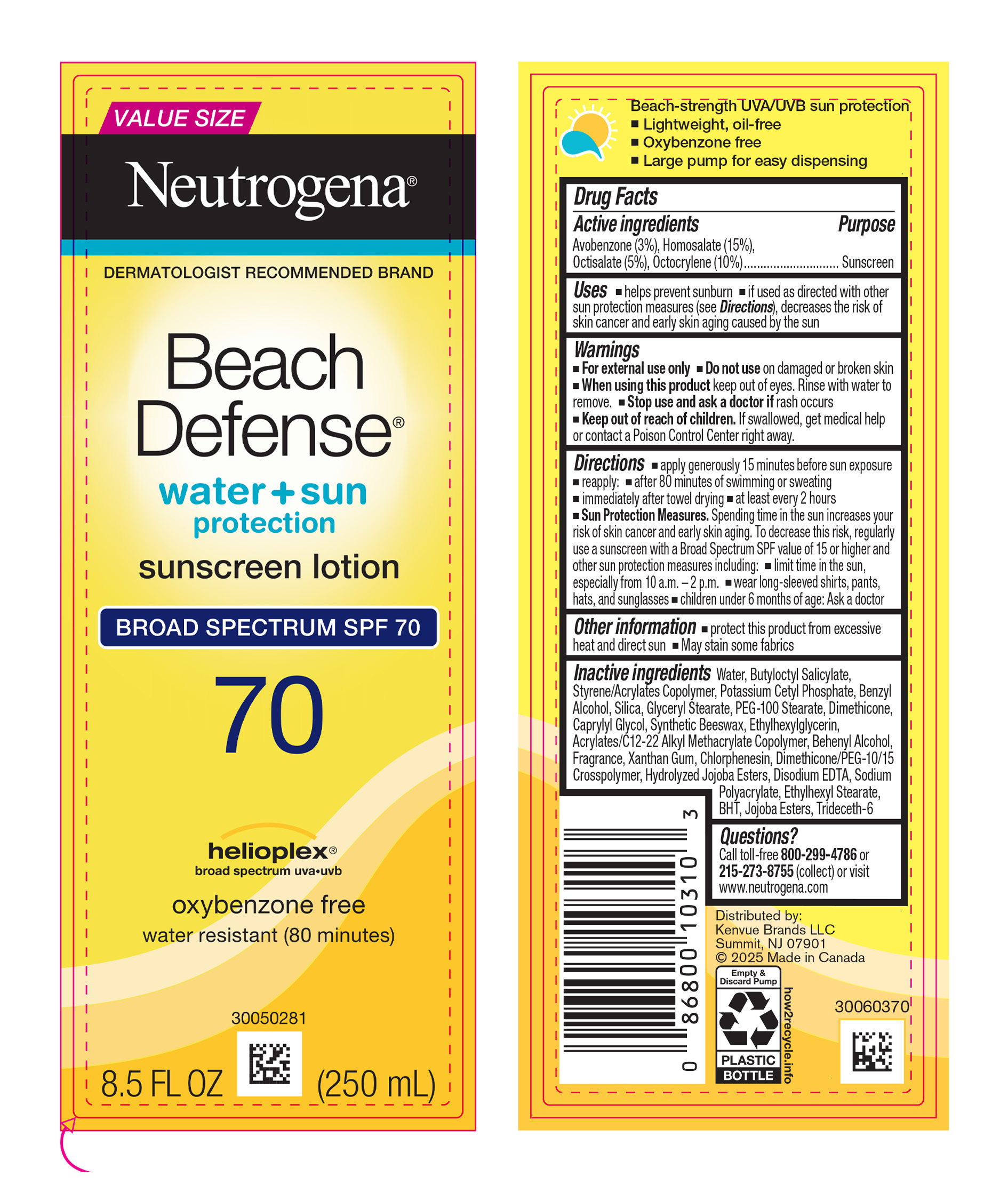 DRUG LABEL: Neutrogena Beach Defense Water Plus Sun Protection Sunscreen Broad Spectrum SPF 70
NDC: 69968-0716 | Form: LOTION
Manufacturer: Kenvue Brands LLC
Category: otc | Type: HUMAN OTC DRUG LABEL
Date: 20250822

ACTIVE INGREDIENTS: AVOBENZONE 30 mg/1 mL; HOMOSALATE 150 mg/1 mL; OCTISALATE 50 mg/1 mL; OCTOCRYLENE 100 mg/1 mL
INACTIVE INGREDIENTS: BUTYL METHACRYLATE/METHYL METHACRYLATE/METHACRYLIC ACID/STYRENE CROSSPOLYMER; POTASSIUM CETYL PHOSPHATE; BENZYL ALCOHOL; SILICON DIOXIDE; GLYCERYL MONOSTEARATE; PEG-100 STEARATE; DIMETHICONE; CAPRYLYL GLYCOL; SYNTHETIC BEESWAX; ETHYLHEXYLGLYCERIN; DOCOSANOL; XANTHAN GUM; CHLORPHENESIN; DIMETHICONE/PEG-10/15 CROSSPOLYMER; HYDROLYZED JOJOBA ESTERS (ACID FORM); EDETATE DISODIUM; ETHYLHEXYL STEARATE; BUTYLATED HYDROXYTOLUENE; JOJOBA OIL, RANDOMIZED; TRIDECETH-6; WATER; BUTYLOCTYL SALICYLATE

Neutrogena® Beach Defense® water + sun protection sunscreen lotion Broad Spectrum SPF 70

Drug Facts

ACTIVE INGREDIENT

Active ingredients | Purpose
Avobenzone 3% | Sunscreen
Homosalate 15% | Sunscreen
Octisalate 5% | Sunscreen
Octocrylene 10% | Sunscreen

Uses

- helps prevent sunburn
- if used as directed with other sun protection measures (see Directions), decreases the risk of skin cancer and early skin aging caused by the sun

Warnings

For external use only

Do not use on damaged or broken skin

When using this product keep out of eyes. Rinse with water to remove.

Stop use and ask a doctor if rash occurs

Keep out of reach of children. If swallowed, get medical help or contact a Poison Control Center right away

Directions

- apply generously 15 minutes before sun exposure
- reapply:
  - after 80 minutes of swimming or sweating
  - immediately after towel drying
  - at least every 2 hours

- Sun Protection Measures. Spending time in the sun increases your risk of skin cancer and early skin aging. To decrease this risk, regularly use a sunscreen with a Broad Spectrum SPF value of 15 or higher and other sun protection measures including:
  - limit time in the sun, especially from 10 a.m. – 2 p.m.
  - wear long-sleeved shirts, pants, hats, and sunglasses
- children under 6 months of age: Ask a doctor

Other information

- protect this product from excessive heat and direct sun
- May stain some fabrics

Inactive ingredients

Water, Butyloctyl Salicylate, Styrene/Acrylates Copolymer, Potassium Cetyl Phosphate, Benzyl Alcohol, Silica, Glyceryl Stearate, PEG-100 Stearate, Dimethicone, Caprylyl Glycol, Synthetic Beeswax, Ethylhexylglycerin, Acrylates/C12-22 Alkyl Methacrylate Copolymer, Behenyl Alcohol, Fragrance, Xanthan Gum, Chlorphenesin, Dimethicone/PEG-10/15 Crosspolymer, Hydrolyzed Jojoba Esters, Disodium EDTA, Sodium Polyacrylate, Ethylhexyl Stearate, BHT, Jojoba Esters, Trideceth-6

Questions?

Call toll-free 800-299-4786 or 215-273-8755 (collect) or visit www.neutrogena.com

Distributed by:

Kenvue Brands LLC

Summit, NJ 07901

PRINCIPAL DISPLAY PANEL - 250 mL Bottle Label

VALUE SIZE
Neutrogena®
DERMATOLOGIST RECOMMENDED BRAND

Beach
Defense®
water + sun
protection
sunscreen lotion

BROAD SPECTRUM SPF 70
70

helioplex®
broad spectrum uva.uvb
oxybenzone free
water resistant (80 minutes)
8.5 FL OZ (250 mL)